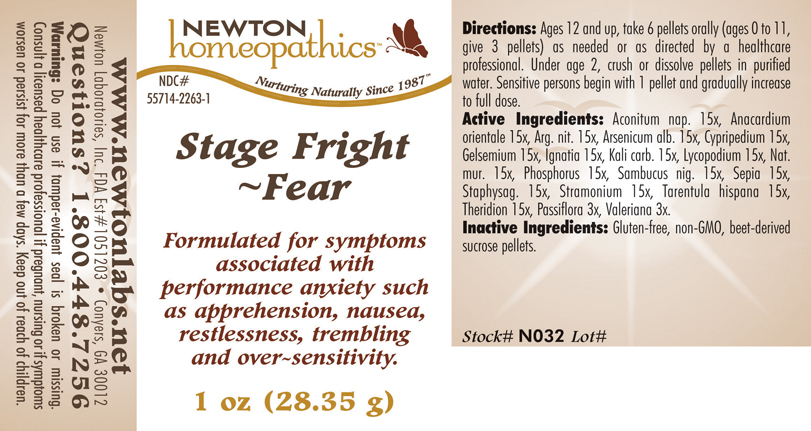 DRUG LABEL: Stage Fright - Fear 
NDC: 55714-2263 | Form: PELLET
Manufacturer: Newton Laboratories, Inc.
Category: homeopathic | Type: HUMAN OTC DRUG LABEL
Date: 20110301

ACTIVE INGREDIENTS: Aconitum Napellus 15 [hp_X]/1 g; Semecarpus Anacardium Juice 15 [hp_X]/1 g; Silver Nitrate 15 [hp_X]/1 g; Arsenic Trioxide 15 [hp_X]/1 g; Cypripedium Parvifolum Root 15 [hp_X]/1 g; Gelsemium Sempervirens Root 15 [hp_X]/1 g; Strychnos Ignatii Seed 15 [hp_X]/1 g; Potassium Carbonate 15 [hp_X]/1 g; Lycopodium Clavatum Spore 15 [hp_X]/1 g; Sodium Chloride 15 [hp_X]/1 g; Phosphorus 15 [hp_X]/1 g; Sambucus Nigra Flowering Top 15 [hp_X]/1 g; Sepia Officinalis Juice 15 [hp_X]/1 g; Delphinium Staphisagria Seed 15 [hp_X]/1 g; Datura Stramonium 15 [hp_X]/1 g; Lycosa Tarantula 15 [hp_X]/1 g; Theridion Curassavicum 15 [hp_X]/1 g; Passiflora Incarnata Flowering Top 3 [hp_X]/1 g; Valerian 3 [hp_X]/1 g
INACTIVE INGREDIENTS: Sucrose

Stage Fright - Fear

INDICATIONS & USAGE SECTION

Stage Fright Fear Formulated for symptoms associated with performance anxiety such as apprehension, nausea, restlessness, trembling and over-sensitivity.

DOSAGE & ADMINISTRATION SECTION

Directions: Ages 12 and up, take 6 pellets orally (ages 0 to 11, give 3 pellets) as needed or as directed by a healthcare professional. Under age 2, crush or dissolve pellets in purified water. Sensitive persons begin with 1 pellet and gradually increase to full dose.

OTC - ACTIVE INGREDIENT SECTION

Aconitum nap. 15x, Anacardium orientale 15x, Arg. nit. 15x, Arsenicum alb. 15x, Cypripedium 15x, Gelsemium 15x, Ignatia 15x, Kali carb. 15x, Lycopodium 15x, Nat.mur. 15x, Phosphorus 15x, Sambucus nig. 15x, Sepia 15x, Staphysag. 15x, Stramonium 15x, Tarentula hispana 15x, Theridion 15x, Passiflora 3x, Valeriana 3x.

OTC - PURPOSE SECTION

Formulated for symptoms associated with performance anxiety such as apprehension, nausea, restlessness, trembling and over-sensitivity.

INACTIVE INGREDIENT SECTION

Inactive Ingredients: Gluten-free, non-GMO, beet-derived sucrose pellets.

QUESTIONS SECTION

www.newtonlabs.net Newton Laboratories, Inc. FDA Est # 1051203 - Conyers, GA 30012
Questions? 1.800.448.7256

WARNINGS SECTION

Warning: Do not use if tamper - evident seal is broken or missing. Consult a licensed healthcare professional if pregnant, nursing or if symptoms worsen or persist for more than a few days. Keep out of reach of children.

OTC - PREGNANCY OR BREAST FEEDING SECTION

Consult a licensed healthcare professional if pregnant, nursing or if symptoms worsen or persist for more than a few days.

OTC - KEEP OUT OF REACH OF CHILDREN SECTION

Keep out of reach of children.